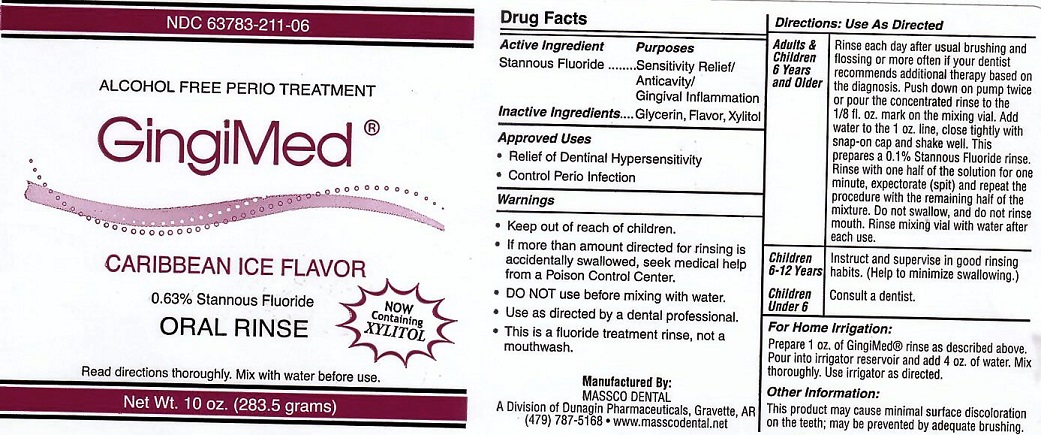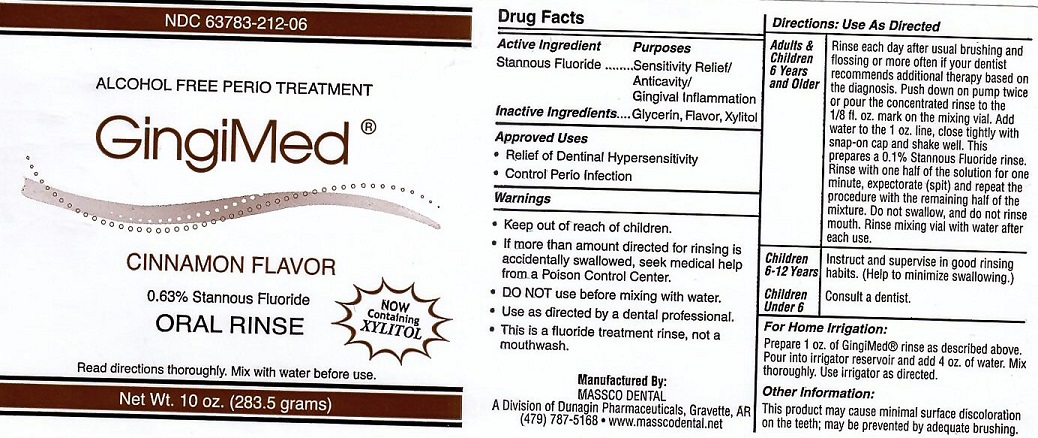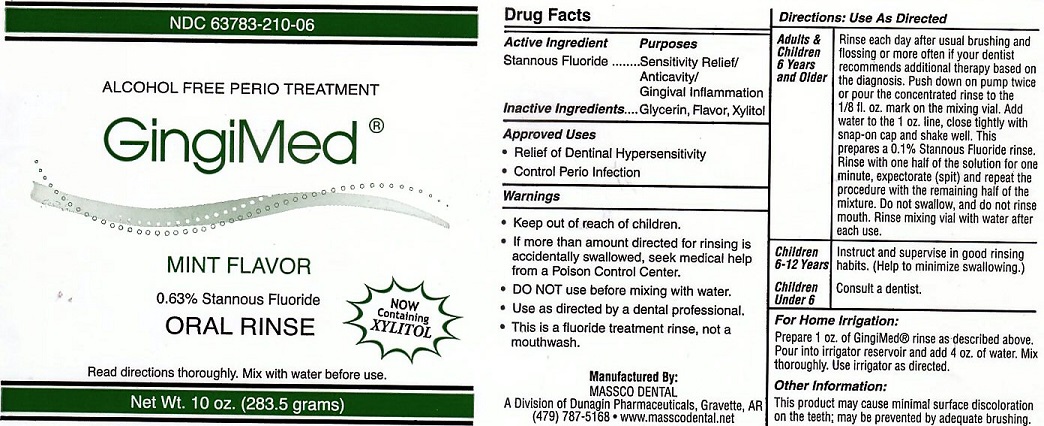 DRUG LABEL: GINGIMED
NDC: 63783-210 | Form: LIQUID
Manufacturer: Massco Dental
Category: prescription | Type: HUMAN PRESCRIPTION DRUG LABEL
Date: 20231217

ACTIVE INGREDIENTS: STANNOUS FLUORIDE 0.19 g/100 g
INACTIVE INGREDIENTS: GLYCERIN; XYLITOL

ACTIVE INGREDIENT

STANNOUS FLUORIDE

INACTIVE INGREDIENTS

GLYCERIN, FLAVOR,XYLITOL

USE

APPROVED USES: RELIEF OF DENTINAL HYPERSENSITIVITY. CONTROL OF PERIO INFECTION.

KEEP OUT OF REACH OF CHILDREN

DIRECTIONS FOR USE

ADULTS AND CHILDREN 6 YEARS AND OLDER: RINSE EACH DAY AFTER USUAL BRUSHING AND FLOSSING OR MORE OFTEN IF YOUR DENTIST RECOMMENDS ADDITIONAL THERAPY BASED ON THE DIAGNOSIS. PUSH DOWN ON PUMP TWICE OR POUR THE CONCENTRATED RINSE TO THE 1/8 FL. OX. MARK ON THE MIXING VIAL. ADD WATER TO THE 1 OZ. LINE. CLOSE TIGHTLY WITH SNAP-ON CAP AND SHAKE WELL. THIS PREPARES A 0.1% STANNOUS FLUORIDE RINSE. RINSE WITH ONE HALF OF THE SOLUTION FOR ONE MINUTE, EXPECTORATE (SPIT) AND REPEAT THE PROCEDURE WITH THE REMAINING HALF OF THE MIXTURE. DO NOT SWALLOW AND DO NOT RINSE MOUTH. RINSE MIXING VIAL WITH WATER AFTER EACH USE.

CHILDREN 6-12 YEARS: INSTRUCT AND SUPERVISE IN GOOD RINSING HABITS. (HELP TO MINIMIZE SWALLOWING)

CHILDREN UNDER 6: CONSULT A DENTIST.

FOR HOME IRRIGATION: PREPARE 1 OZ. OF GINGIMED RINSE AS DESCRIBED ABOVE. POUR INTO IRRIGATOR RESIVOIR AND ADD 4 OZ. OF WATER. MIX THOROUGHLY. USE IRRIGATOR AS DESCRIBED

OTHER INFORMATION

THIS PRODUCT MAY CAUSE MINIMAL SURFACE DISCOLORATION ON THE TEETH, MAY BE PREVENTED BY ADEQUATE BRUSHING.

WARNINGS

IF MORE THAN AMOUNT DIRECTED FOR RINSING IS ACCIDENTALLY SWALLOWED, SEEK MEDICAL HELP FROM A POISON CONTROL CENTER. DO NOT USE BEFORE MIXING WITH WATER. USE AS DIRECTED BY A DENTAL PROFESSIONAL. THIS IS A FLUORIDE TREATMENT RINSE, NOT A MOUTHWASH.

PACKAGE LABEL

ALCOHOL FREE PERIO TREATMENT. GINGIMED 0.63% STANNOUS FLUORIDE READ DIRECTIONS THOROUGHLY. MIX WITH WATER BEFORE USE. NOW CONTAINING XYLITOL

MANUFACTURED BY MASSCO DENTAL A DIVISION OF DUNAGIN PHARMACEUTICALS, GRAVETTE, AR (479) 787-5168 WWW.MASSCODENTAL.NET

res